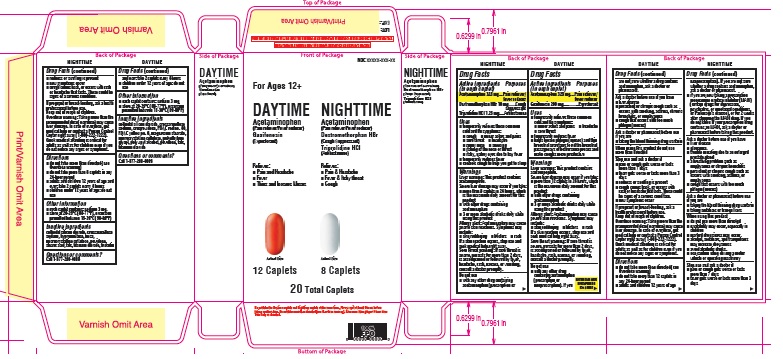 DRUG LABEL: Daytime Nighttime
NDC: 41226-678 | Form: KIT | Route: ORAL
Manufacturer: KROGER COMPANY
Category: otc | Type: HUMAN OTC DRUG LABEL
Date: 20250708

ACTIVE INGREDIENTS: ACETAMINOPHEN 325 mg/1 1; GUAIFENESIN 200 mg/1 1; ACETAMINOPHEN 325 mg/1 1; DEXTROMETHORPHAN HYDROBROMIDE 10 mg/1 1; TRIPROLIDINE HYDROCHLORIDE 1.25 mg/1 1
INACTIVE INGREDIENTS: CROSCARMELLOSE SODIUM; CROSPOVIDONE; FD&C YELLOW NO. 6; FD&C RED NO. 40; MAGNESIUM STEARATE; MICROCRYSTALLINE CELLULOSE; POLYETHYLENE GLYCOL, UNSPECIFIED; POVIDONE, UNSPECIFIED; TALC; TITANIUM DIOXIDE; SILICON DIOXIDE; POLYVINYL ALCOHOL; CROSCARMELLOSE SODIUM; MICA; MICROCRYSTALLINE CELLULOSE; POVIDONE, UNSPECIFIED; SILICON DIOXIDE; STEARIC ACID; TALC; TITANIUM DIOXIDE; HYPROMELLOSE, UNSPECIFIED; TRIACETIN

Kroger Daytime Nighttime Multisymptom Relief Tablets

Drug Facts

ACTIVE INGREDIENT

Daytime

Active ingredients (in each caplet)

Acetaminophen 325 mg

Guaifenesin 200 mg

Nighttime

Active ingredients (in each caplet)

Acetaminophen 325 mg

Dextromethorphan HBr 10 mg

Triprolidine HCl 1.25 mg

PURPOSE

Daytime

Pain reliever/fever reducer

Expectorant

Nighttime

Pain reliever/fever reducer

Cough suppressant

Antihistamine

INDICATIONS AND USAGE

Daytime

temporarily relieves these common cold and flu symptoms:

- minor aches and pains
- headache
- sore throat

helps loosen phlegm (mucus) and thin bronchial secretions to rid the bronchial passageways of bothersome mucus and make coughs more productive
temporarily reduces fever

Nighttime

temporarily relieves these common cold and flu symptoms:

- cough
- minor aches and pains
- sore throat
- headache
- runny nose
- sneezing
- itching of the nose or throat
- itchy, watery eyes due to hay fever

temporarily reduces fever
controls cough to help you get to sleep

Warnings

Liver warning: This product contains acetaminophen.

Severe liver damage may occur if you take:

- more than 12 caplets in 24 hours, which is the maximum daily amount for this product
- with other drugs containing acetaminophen
- 3 or more alcoholic drinks daily while using this product

Allergy alert: Acetaminophen may cause severe skin reactions. Symptoms may include:

- skin reddening
- blisters
- rash

If a skin reaction occurs, stop use and seek medical help right away.

Sore throat warning: If sore throat is severe, persists for more than 2 days, is accompanied or followed by fever, headache, rash, nausea, or vomiting, consult a doctor promptly.

Do not use

Daytime

- with any other drug containing acetaminophen (prescription or nonprescription). If you are not sure whether a drug contains acetaminophen, ask a doctor or pharmacist.

Nighttime

- with any other drug containing acetaminophen (prescription or nonprescription). If you are not sure whether a drug contains acetaminophen, ask a doctor or pharmacist.
- if you are now taking a prescription monoamine oxidase inhibitor (MAOI) (certain drugs for depression, psychiatric, or emotional conditions, or Parkinson's disease), or for 2 weeks after stopping the MAOI drug. If you do not know if your prescription drug contains an MAOI, ask a doctor or pharmacist before taking this product.

Ask a doctor before use if you have

Daytime

- liver disease
- persistent or chronic cough such as occurs with smoking, asthma, chronic bronchitis, or emphysema
- cough that occurs with too much phlegm (mucus)

Nighttime

- liver disease
- glaucoma
- trouble urinating due to an enlarged prostate gland
- a breathing problem such as emphysema or chronic bronchitis
- persistent or chronic cough such as occurs with smoking, asthma, or emphysema
- cough that occurs with too much phlegm (mucus)

Ask a doctor or pharmacist before use

Daytime

- if you are taking the blood thinning drug warfarin

Nighttime

- taking the blood thinning drug warfarin
- taking sedatives or tranquilizers

When using this product

Daytime

- do not use more than directed

Nighttime

- do not use more than directed
- excitability may occur, especially in children
- marked drowsiness may occur
- alcohol, sedatives, and tranquilizers may increase drowsiness
- avoid alcoholic drinks
- use caution when driving a motor vehicle or operating machinery

Stop use and ask a doctor if

Daytime

- pain or cough gets worse or lasts more than 7 days
- fever gets worse or lasts more than 3 days
- redness or swelling is present
- cough comes back, or occurs with fever, rash, or headache that lasts. These could be signs of a serious condition.
- new symptoms occur

Nighttime

- pain or cough gets worse or lasts more than 7 days
- fever gets worse or lasts more than 3 days
- redness or swelling is present
- new symptoms occur
- cough comes back, or occurs with rash or headache that lasts. These could be signs of a serious condition.

PREGNANCY OR BREAST FEEDING

If pregnant or breast-feeding, ask a health professional before use.

Keep out of reach of children.

Overdose warning: Taking more than the recommended dose (overdose) may cause liver damage. In case of overdose, get medical help or contact a Poison Control Center right away (1-800-222-1222). Quick medical attention is critical for adults as well as for children even if you do not notice any signs or symptoms.

Directions

Daytime

- do not take more than directed (see Overdose warning)
- do not take more than 12 caplets in any 24-hour period
- adults and children 12 years of age and over: take 2 caplets every 4 hours
- children under 12 years of age: do not use

Nighttime

- do not take more than directed (see Overdose warning)
- do not take more than 8 caplets in any 24-hour period
- adults and children 12 years of age and over: take 2 caplets every 4 hours
- children under 12 years of age: do not use

Other information

- each caplet contains: sodium 3 mg
- store at 20-25°C (68-77°F), excursion permitted between 15-30°C (59-86°F)

Inactive ingredients Daytime

colloidal silicon dioxide, croscarmellose sodium, crospovidone, FD&C red no. 40, FD&C yellow no. 6, magnesium stearate, microcrystalline cellulose, polyethylene glycol, polyvinyl alcohol, povidone, talc, titanium dioxide

Inactive ingredients Nighttime

colloidal silicon dioxide, croscarmellose sodium, hypromellose, mica, microcrystalline cellulose, povidone, stearic acid, talc, titanium dioxide, triacetin

Questions or comments?

Call 1-800-632-6900